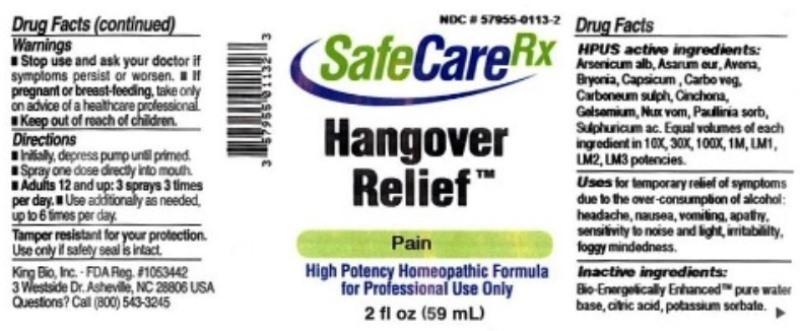 DRUG LABEL: Hangover Relief
NDC: 57955-0113 | Form: LIQUID
Manufacturer: King Bio Inc.
Category: homeopathic | Type: HUMAN OTC DRUG LABEL
Date: 20150319

ACTIVE INGREDIENTS: ARSENIC TRIOXIDE 10 [hp_X]/59 mL; ASARUM EUROPAEUM 10 [hp_X]/59 mL; AVENA SATIVA FLOWERING TOP 10 [hp_X]/59 mL; BRYONIA ALBA ROOT 10 [hp_X]/59 mL; CAPSICUM 10 [hp_X]/59 mL; ACTIVATED CHARCOAL 10 [hp_X]/59 mL; CARBON DISULFIDE 10 [hp_X]/59 mL; CINCHONA OFFICINALIS BARK 10 [hp_X]/59 mL; GELSEMIUM SEMPERVIRENS ROOT 10 [hp_X]/59 mL; STRYCHNOS NUX-VOMICA SEED 10 [hp_X]/59 mL; PAULLINIA CUPANA SEED 10 [hp_X]/59 mL; SULFURIC ACID 10 [hp_X]/59 mL
INACTIVE INGREDIENTS: WATER; ANHYDROUS CITRIC ACID; POTASSIUM SORBATE

Hangover Relief™

ACTIVE INGREDIENT

Drug Facts__________________________________________________________________________________________________________

HPUS active ingredients: Arsenicum album, Asarum europaeum, Avena sativa, Bryonia, Capsicum annuum, Carbo vegetabilis, Carboneum sulphuratum, Cinchona officinalis, Gelsemium sempervirens, Nux vomica, Paullinia sorbilis, Sulphuricum acidum. Equal volumes of each ingredient in 10X, 30X, 100X, 1M, LM1, LM2, LM3 potencies.

INDICATIONS AND USAGE

Uses for temporary relief of symptoms due to the over consumption of alcohol: headache, nausea, vomiting, apathy, sensitivity to noise and light, irritability, foggy mindedness.

Inactive Ingredients:

Bio-Energetically Enhanced™ pure water, citric acid and potassium sorbate.

Warnings

- Stop use and ask your doctor if symptoms persist or worsen.
- If pregnant or breast-feeding, take only on advice of a healthcare professional.

- Keep out of reach of children.

Directions

- Initially, depress pump until primed.
- Spray one dose directly into mouth.
- Adults 12 and up: 3 sprays 3 times per day.
- Use additionaly as needed, up to 6 times per day.

OTHER SAFETY INFORMATION

Tamper resistant for your protection. Use only if safety seal is intact.

PURPOSE

Uses for temporary relief of symptoms due to the over consumption of alcohol:

- headache
- nausea
- vomiting
- apathy
- sensitivity to noise and light
- irritability
- foggy mindedness